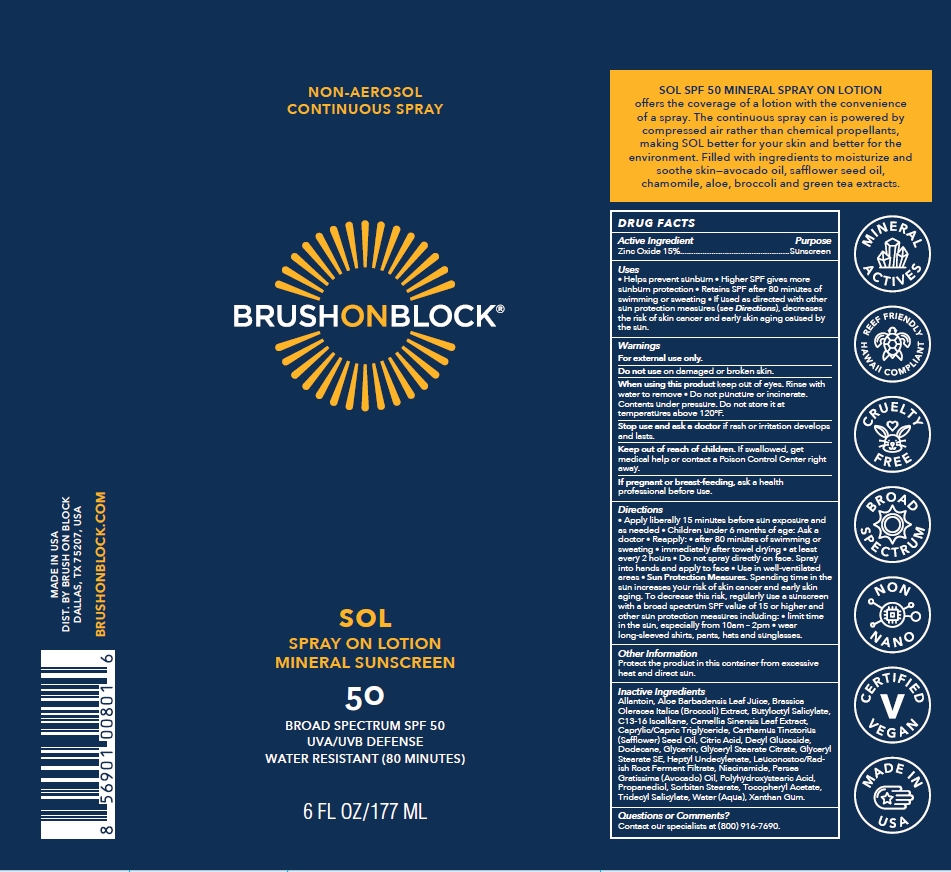 DRUG LABEL: BRUSH ON BLOCK SPF 50 MINERAL
NDC: 58274-026 | Form: SPRAY
Manufacturer: SPF Ventures, LLC
Category: otc | Type: HUMAN OTC DRUG LABEL
Date: 20250227

ACTIVE INGREDIENTS: ZINC OXIDE 15 g/100 mL
INACTIVE INGREDIENTS: ALOE BARBADENSIS LEAF; C13-16 ISOPARAFFIN; CAPRYLIC/CAPRIC TRIGLYCERIDE; CITRIC ACID; DECYL GLUCOSIDE; DODECANE; GLYCERIN; HEPTYL UNDECYLENATE; NIACINAMIDE; AVOCADO OIL; SORBITAN STEARATE; TRIDECYL SALICYLATE; XANTHAN GUM; LEUCONOSTOC/RADISH ROOT FERMENT FILTRATE; ALLANTOIN; CARTHAMUS TINCTORIUS (SAFFLOWER) SEED OIL; CAMELLIA SINENSIS LEAF; GLYCERYL STEARATE SE; BUTYLOCTYL SALICYLATE; PROPANEDIOL; WATER; GLYCERYL STEARATE CITRATE; .ALPHA.-TOCOPHEROL ACETATE, D-; POLYHYDROXYSTEARIC ACID (2300 MW); BROCCOLI SPROUT

BRUSH ON BLOCK SPF 50 MINERAL SPRAY

Active ingredients

ZINC OXIDE 15%

Purpose

Sunscreen

Uses

- Helps prevent sunburn
- Higher SPF gives more sunburn protection
- Retains SPF after 80 minutes of swimming or sweating
- If used as directed with other sun protection measure (see Directions), decreases the risk of skin cancer and early skin aging caused by the sun.

Warnings

For external use only.

Do not use on damaged or broken skin.

When using this product keep out of eyes. Rinse with water to remove.

Do not puncture or incinerate. Contents under pressure. Do not store it at temperatures above 120F.

Stop use and ask a doctor if rash or irritation develops and lasts.

Keep out of reach of children

If product is swallowed, get medical help or contact a Poison Control Center right away.

If pregnant or breast-feeding, ask a health professional before use.

Directions

- Apply liberally 15 minutes before sun exposure and as needed;
- Children under 6 months of age: ask a doctor
- Reapply: After 80 minutes of swimming or sweating; Immediately after towel drying; At least every 2 hours; Do not spray directly on face. Spray into hands and apply to face; Use in well-ventilated areas;

Sun Protection Measures. Spending time in the sun increases your risk of skin cancer and early skin aging. To decrease this risk, regularly use a sunscreen with a broad spectrum SPF value of 15 or higher and other sun protection measures including: Limit time in the sun, especially from 10am-2pm; Wear long-sleeved shirts, pants, hats and sunglasses;

Inactive ingredients

ALLANTOIN

ALOE BARBADENSIS LEAF JUICE

BRASSICA OLERACEA ITALICA (BROCCOLI) EXTRACT

BUTYLOCTYL SALICYLATE

C13-16 ISOALKANE

CAMELLIA SINENSIS LEAF EXTRACT

CAPRYLIC/CAPRIC TRIGLYCERIDE

CARTHAMUS TINCTORIOUS (SAFFLOWER) SEED OIL

CITRIC ACID

DECYL GLUCOSIDE

DODECANE

GLYCERIN

GLYCERYL STEARATE CITRATE

GLYCERYL STEARATE SE

HEPTYL UNDECYLENATE

LEUCONOSTOC/RADISH ROOT FERMENT FILTRATE

NIACINAMIDE

PERSEA GRATISSIMA (AVOCADO) OIL

POLYHYDROXYSTEARIC ACID

PROPANEDIOL

SORBITAN STEARATE

TOCOPHERYL ACETATE

TRIDECYL SALICYLATE

WATER (AQUA)

XANTHAN GUM

Other Information

Protect the product in this container from excessive heat and direct sun.